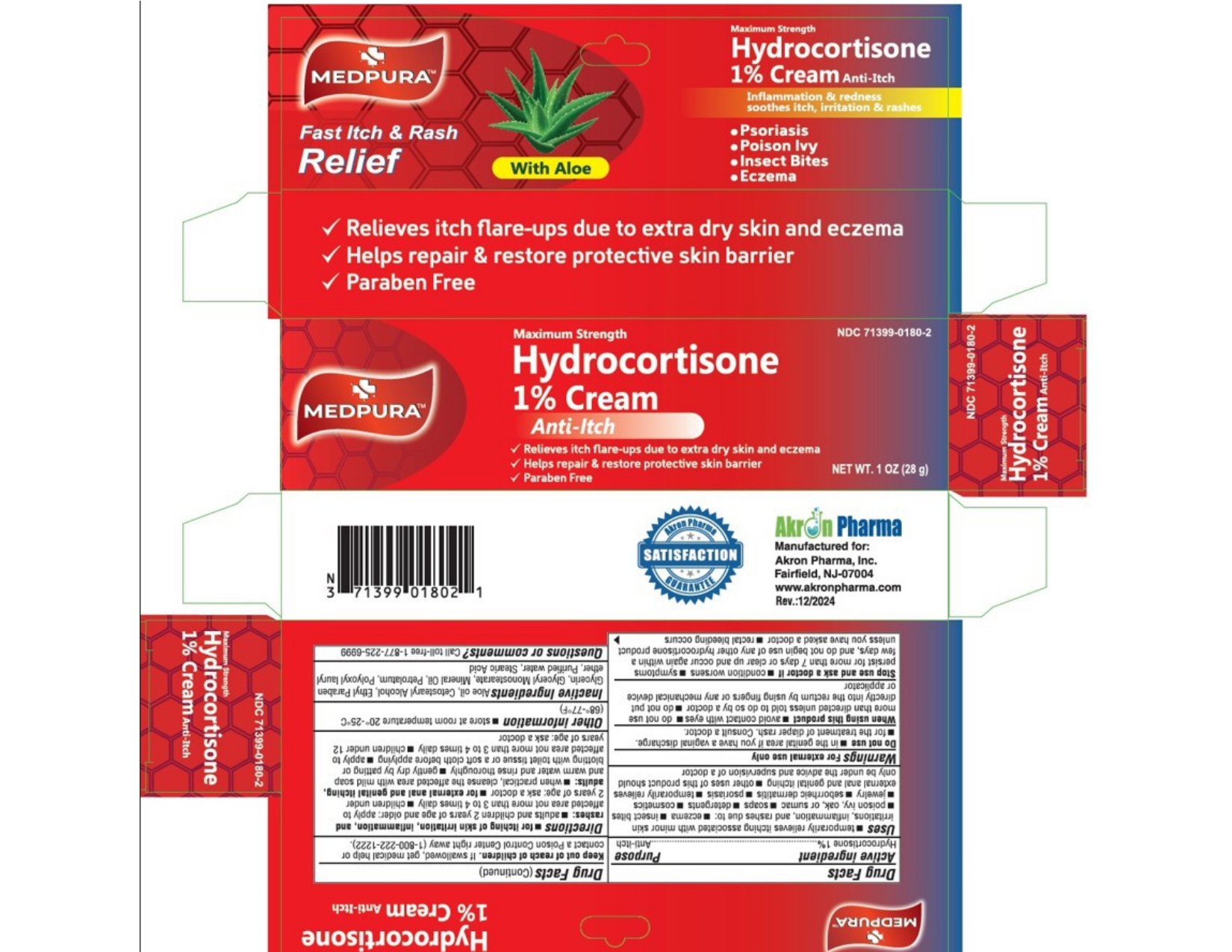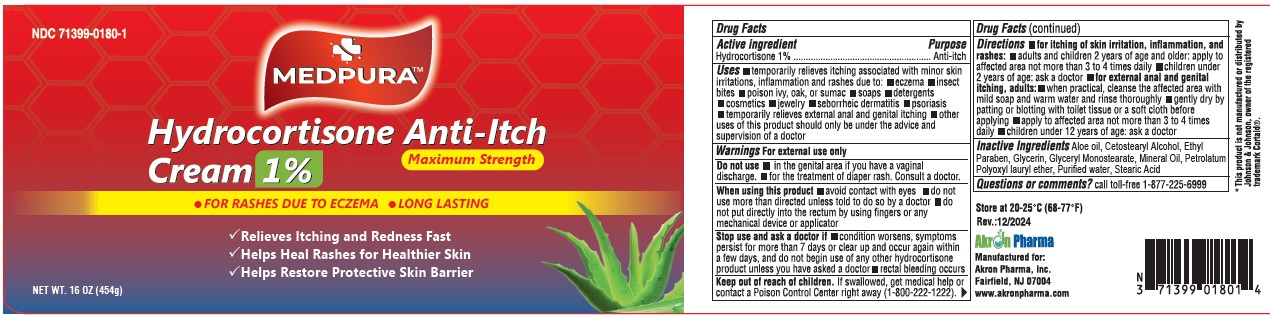 DRUG LABEL: Hydrocortisone
NDC: 71399-0180 | Form: CREAM
Manufacturer: AKRON PHARMA INC
Category: otc | Type: HUMAN OTC DRUG LABEL
Date: 20251229

ACTIVE INGREDIENTS: HYDROCORTISONE 1 mg/100 g
INACTIVE INGREDIENTS: ALOE; CETOSTEARYL ALCOHOL; ETHYLPARABEN; GLYCERIN; GLYCERYL MONOSTEARATE; MINERAL OIL; PETROLATUM; LAURETH-23; WATER; STEARIC ACID

MEDPURA
Hydrocortisone Anti-Itch Cream 1%
Maximum Strength
with ALOE
Drug Facts

Active Ingredient

Hydrocortisone 1%

Purpose

Anti-itch

Uses

temporarily relieves itching associated with minor skin irritations, inflammation and rashes due to:

- eczema
- insect bites
- poison ivy, oak or sumac
- soaps
- detergents
- cosmetics
- jewelry,
- seborrheic dermatitis
- psoriasis
- temporarily relieves external anal and genital itching
- Other uses of this product should only be under the advice and supervision of a doctor.

Warnings

For external use only.

Do not use

- in the genital area if you have a vaginal discharge.
- for the treatment of diaper rash, Consult a doctor.

When using this product

- avoid contact with eyes
- do not use more than directed unless told to do so by a doctor
- do not put directly into the rectum by using fingers or any mechanical device or applicator

Stop use and ask a doctor if

- Condition worsens
- symptoms persist for more than 7 days or clear up and occur again within a few days, and do not begin use of any other hydrocortisone product unless you have asked a doctor
- rectal bleeding occurs.

Keep out of Reach of Children

If swallowed, get medical help or contact Poison Control Center right away (1-800-222-1222).

Directions

for itching of skin irritation, inflammation, and rashes:

- adults and children 2 years of age and older: apply to affected area not more than 3 to 4 times daily
- children under 2 years of age: ask a doctor

for external anal and genital itching, adults:

- when practical, cleanse the affected area with mild soap and warm water and rinse thoroughly
- gently dry by patting or blotting with toilet tissue or a soft cloth before applying
- apply to affected area not more than 3 to 4 times daily
- children under 12 years of age: ask a doctor

Other Information

store at room temperature 20^0-25^0C (68^0-77^0F).

Inactive Ingredients

Aloe oil, Cetostearyl Alcohol, Ethylparaben, Glycerin, Glyceryl Monostearate, Mineral Oil, Petrolatum, Polyoxyl lauryl ether, Purified water, Stearic Acid

Questions or Comments?

Call toll-free 1-877-225-6999

Manufactured for:

Akron Pharma, Inc.
Fairfield, NJ 07004

www.akronpharma.com